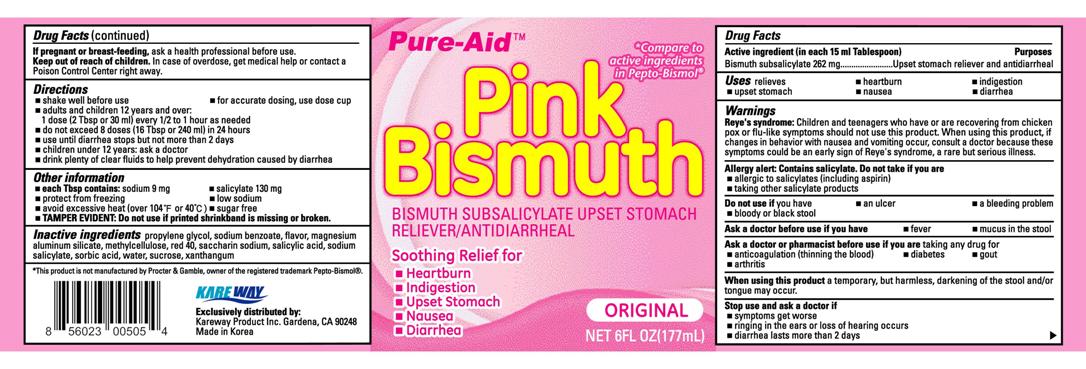 DRUG LABEL: Pink Bismuth
NDC: 67510-0505 | Form: LIQUID
Manufacturer: Kareway Product, Inc.
Category: otc | Type: HUMAN OTC DRUG LABEL
Date: 20110829

ACTIVE INGREDIENTS: BISMUTH SUBSALICYLATE 262 mg/15 mL
INACTIVE INGREDIENTS: PROPYLENE GLYCOL; SODIUM BENZOATE; MAGNESIUM ALUMINUM SILICATE; METHYLCELLULOSE (100 CPS); FD&C RED NO. 40; SACCHARIN SODIUM; SALICYLIC ACID; SODIUM SALICYLATE; SORBIC ACID; WATER; SUCROSE; XANTHAN GUM

Drug Facts

Active ingredient (in each 15 ml Tablespoon)

Bismuth subsalicylate 262 mg

Purpose

Upset stomach reliever and antidiarrheal

Uses

relieves

- heartburn
- indigestion
- upset stomach
- nausea
- diarrhea

Warnings

Reye's syndrome:

Children and teenagers who have or are recovering from chicken pox or flu-like symptoms should not use this product. When using this product, if changes in behavior with nausea and vomiting occur, consult a doctor because these symptoms could be an early sign of Reyes syndrome, a rare but serious illness.

Allergy alert:

Contains salicylate. Do not take if you are

- allergic to salicylates (including aspirin)
- taking other salicylate products

Do not use if

you have

- an ulcer
- a bleeding problem
- bloody or black stool

Ask a doctor before use if you have

- fever
- mucus in the stool

Ask a doctor or pharmacist before use if you are

taking any drug for

- anticoagulation (thinning the blood)
- diabetes
- gout
- arthritis

When using this product

a temporary, but harmless, darkening of the stool and/or tongue may occur.

Stop use and ask a doctor if

- symptoms get worse
- ringing in the ears or loss of hearing occurs
- diarrhea lasts more than 2 days

If pregnant or breast-feeding,

ask a health professional before use.

Keep out of reach of children.

In case of overdose, get medical help or contact a Poison Control Center right away.

Directions

- shake well before use
- for accurate dosing, use dose cup
- adults and children 12 years and over: 1 dose (2Tbsp or 30 ml) every 1/2 to 1 hour as needed
- do not exceed 8 doses (16 Tbsp or 240 ml) in 24 hours
- use until diarrhea stops but not more than 2 days
- children under 12 years: ask a doctor
- drink plenty of clear fluids to help prevent dehydration caused by diarrhea

Other information

- each Tspb contains: sodium 9 mg
- salicylate 130 mg
- protect from freezing
- low sodium
- avoid excessive heat (over 104°F or 40°C)
- sugar free
- TAMPER EVIDENT: Do not use if printed shrinkband is missing or broken.

Inactive ingredients

propylene glycol, sodium benzoate, flavor, magnesium aluminum silicate, methylcellulose, red 40, saccharin sodium, salicylic acid, sodium slicylate, sorbic acid, water, sucrose, xanthan gum

Package label

Pink Bismuth